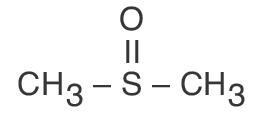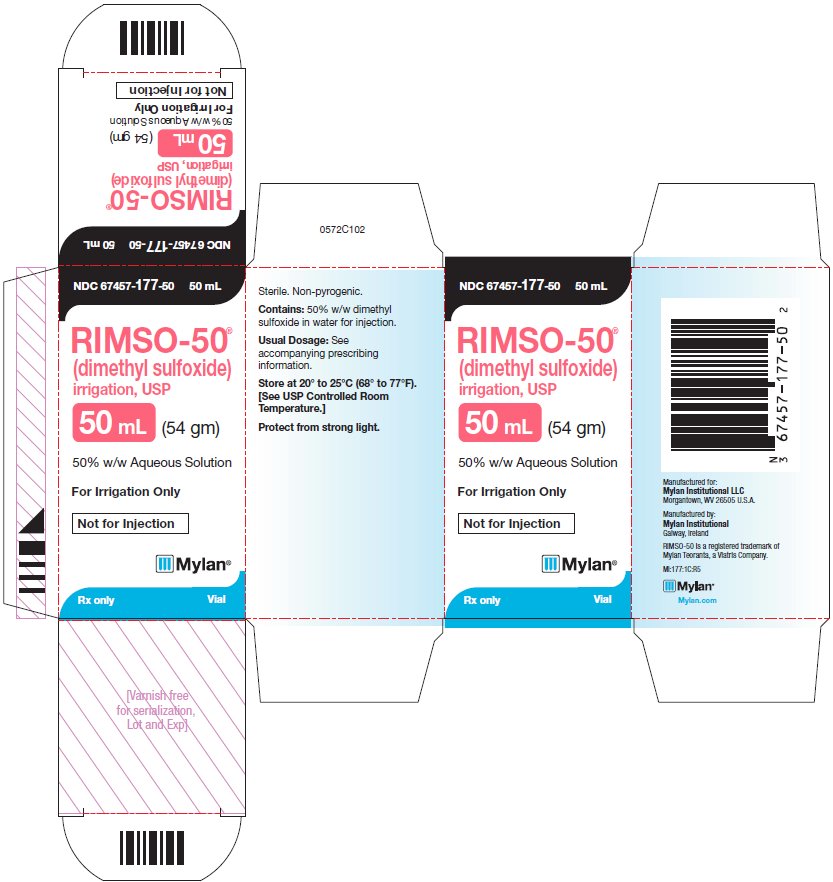 DRUG LABEL: RIMSO-50
NDC: 67457-177 | Form: IRRIGANT
Manufacturer: Mylan Institutional LLC
Category: prescription | Type: HUMAN PRESCRIPTION DRUG LABEL
Date: 20210317

ACTIVE INGREDIENTS: Dimethyl Sulfoxide 0.54 g/1 mL
INACTIVE INGREDIENTS: WATER

RIMSO-50®
brand of dimethyl sulfoxide irrigation, USP

PRESCRIBING INFORMATION

Rx only

DESCRIPTION

RIMSO-50®(dimethyl sulfoxide) (DMSO) 50% w/w Aqueous Solution for intravesical instillation.

Each mL contains 0.54 gm dimethyl sulfoxide STERILE AND NON-PYROGENIC.

Intravesical instillation for the treatment of interstitial cystitis.

NOT FOR INTRAMUSCULAR OR INTRAVENOUS INJECTION.

The active component of RIMSO-50® is dimethyl sulfoxide which has the empirical formula C2H6OS, and is structurally represented as:

Dimethyl sulfoxide is a clear, colorless and essentially odorless liquid which is miscible with water and most organic solvents. Other physical characteristics include: molecular weight 78.13, melting point 18.3° C, and a specific gravity of 1.096.

CLINICAL PHARMACOLOGY

Dimethyl sulfoxide is metabolised in man by oxidation to dimethyl sulfone or by reduction to dimethyl sulfide. Dimethyl sulfoxide and dimethyl sulfone are excreted in the urine and feces. Dimethyl sulfide is eliminated through the breath and skin and is responsible for the characteristic odor from patients on dimethyl sulfoxide medication. Dimethyl sulfone can persist in serum for longer than two weeks after a single intravesical instillation. No residual accumulation of dimethyl sulfoxide has occurred in man or lower animals who have received treatment for protracted periods of time. Following topical application, dimethyl sulfoxide is absorbed and generally distributed in the tissues and body fluids.

INDICATIONS AND USAGE

RIMSO-50® (dimethyl sulfoxide) is indicated for the symptomatic relief of patients with interstitial cystitis. RIMSO-50® has not been approved as being safe and effective for any other indication. There is no clinical evidence of effectiveness of dimethyl sulfoxide in the treatment of bacterial infections of the urinary tract.

CONTRAINDICATIONS

None known.

WARNINGS

Dimethyl sulfoxide can initiate the liberation of histamine and there has been occasional hypersensitivity reaction with topical administration of dimethyl sulfoxide. This hypersensitivity has been reported in one patients receiving intravesical RIMSO-50®. The physician should be cognizant of this possibility in prescribing RIMSO-50®. If anaphylactoid symptoms develop, appropriate therapy should be instituted.

PRECAUTIONS

Changes in the refractive index and lens opacities have been seen in monkeys, dogs and rabbits given high doses of dimethyl sulfoxide chronically. Since lens changes were noted in animals, full eye evaluations, including slit lamp examinations, are recommended prior to and periodically during treatment.

Approximately every six months patients receiving dimethyl sulfoxide should have a biochemical screening, particularly liver and renal function tests, and complete blood count.

Intravesical instillation of RIMSO-50® may be harmful to patients with urinary tract malignancy because of dimethyl sulfoxide-induced vasodilation.

Some data indicate that dimethyl sulfoxide potentiates other concomitantly administered medications.

Dimethyl sulfoxide caused teratogenic responses in hamsters, rats and mice when administered intraperitoneally at high doses (2.5 to 12 gm/kg). Oral or topical doses of dimethyl sulfoxide did not cause problems of reproduction in rats, mice and hamsters. Topical doses (5 gm/kg first two days, then 2.5 gm/kg - last eight days) produced terata in rabbits, but in another study, topical doses of 1.1 gm/kg days 3 through 16 of gestation failed to produce any abnormalities. There are no adequate and well controlled studies in pregnant women. Dimethyl sulfoxide should be used during pregnancy only if the potential benefit justifies the potential risk to the fetus.

It is not known whether this drug is excreted in human milk. Because many drugs are excreted in human milk, caution should be exercised when dimethyl sulfoxide is administered to a nursing woman.

Safety and effectiveness in children have not been established.

Information available to be given to the patient is reprinted at the end of this text.

ADVERSE REACTIONS

A garlic-like taste may be noted by the patient within a few minutes after instillation of RIMSO-50® (dimethyl sulfoxide). This taste may last several hours and because of the presence of metabolites, an odor on the breath and skin may remain for 72 hours.

Transient chemical cystitis has been noted following instillation of dimethyl sulfoxide.

The patient may experience moderately severe discomfort on administration. Usually this becomes less prominent with repeated administration.

DRUG ABUSE AND DEPENDENCE

None known.

OVERDOSAGE

The oral LD50 of dimethyl sulfoxide in the dog is greater than 10 gm/kg. It is improbable that this dosage level could be obtained with intravesical instillation of RIMSO-50® in the patient.

In case of accidental oral ingestion, specific measures should be taken to induce emesis. Additional measures which may be considered are gastric lavage, activated charcoal and force diuresis.

DOSAGE AND ADMINISTRATION

Instillation of 50 mL of RIMSO-50® (dimethyl sulfoxide) directly into the bladder may be accomplished by catheter or asepto syringe and allow to remain for 15 minutes. Application of an analgesic lubricant gel such as lidocaine jelly to the urethra is suggested prior to insertion of the catheter to avoid spasm. The medication is expelled by spontaneous voiding. It is recommended that the treatment be repeated every two weeks until maximum symptomatic relief is obtained. Thereafter, time intervals between therapy may be increased appropriately.

Administration of oral analgesic medication or suppositories containing belladonna and opium prior to the instillation of RIMSO-50® can reduce bladder spasm.

In patients with severe interstitial cystitis with very sensitive bladders, the initial treatment, and possibly the second and third (depending on patient response) should be done under anesthesia. (Saddle block has been suggested).

HOW SUPPLIED

Vials contain 50 mL of sterile and non-pyrogenic RIMSO-50® (50% w/w dimethyl sulfoxide aqueous solution).

Dimethyl sulfoxide is clear and colorless.

NDC 67457-177-50
carton containing a 50 mL vial

STORAGE AND HANDLING

Store at 20° to 25°C (68° to 77°F). [See USP Controlled Room Temperature.]

Protect from strong light.

For additional information concerning RIMSO-50®, contact Mylan Institutional LLC, Morgantown, WV 26505.

Manufactured for:
Mylan Institutional LLC
Morgantown, WV 26505 U.S.A.

Manufactured by:
Mylan Institutional
Galway, Ireland

INFORMATION FOR PATIENTS (Physician Copy)

RIMSO-50® is a sterile solution of 50% dimethyl sulfoxide (DMSO) and 50% water that has been approved by the U.S. Food and Drug Administration for use in the symptomatic relief of patients with interstitial cystitis.

RIMSO-50® will be instilled in the bladder on an inpatient or out-patient basis, which will be determined by your physician.

Some data indicate that dimethyl sulfoxide could change the effectiveness of medication(s) that you may be presently receiving. Be sure to mention the name and dosage of all medicines you are taking to your physician before a RIMSO-50® instillation.

A garlic-like taste may be noted by the patient within a few minutes after instillation of RIMSO-50® (dimethyl sulfoxide). This taste may last several hours. An odor on the breath and skin may be present and remain for up to 72 hours.

Some patients may experience discomfort on administration of the drug. Usually this becomes less prominent with repeated administration.

If you are pregnant or nursing, ask your physician about the advisability of using RIMSO-50®.

Some eye changes have been observed in animals treated with DMSO in large doses for prolonged periods. Therefore your doctor may want you to have eye evaluations, including slit lamp examinations prior to and periodically during treatment.

RIMSO-50®
(dimethyl sulfoxide)
irrigation, USP 1013L102

Mylan Institutional LLC
Morgantown, WV 26505 U.S.A.

Revised: 3/2021
MI:RIMSIG:R5

RIMSO-50 is a registered trademark of Mylan Teoranta, a Viatris Company.

INFORMATION FOR PATIENTS (Patient Copy)

RIMSO-50® is a sterile solution of 50% dimethyl sulfoxide (DMSO) and 50% water that has been approved by the U.S. Food and Drug Administration for use in the symptomatic relief of patients with interstitial cystitis.

RIMSO-50® will be instilled in the bladder on an inpatient or out-patient basis, which will be determined by your physician.

Some data indicate that dimethyl sulfoxide could change the effectiveness of medication(s) that you may be presently receiving. Be sure to mention the name and dosage of all medicines you are taking to your physician before a RIMSO-50® instillation.

A garlic-like taste may be noted by the patient within a few minutes after instillation of RIMSO-50® (dimethyl sulfoxide). This taste may last several hours. An odor on the breath and skin may be present and remain for up to 72 hours.

Some patients may experience discomfort on administration of the drug. Usually this becomes less prominent with repeated administration.

If you are pregnant or nursing, ask your physician about the advisability of using RIMSO-50®.

Some eye changes have been observed in animals treated with DMSO in large doses for prolonged periods. Therefore your doctor may want you to have eye evaluations, including slit lamp examinations prior to and periodically during treatment.

PRINCIPAL DISPLAY PANEL - 50 mL Vial

NDC 67457-177-50 50 mL

RIMSO-50®
(dimethyl sulfoxide)
irrigation, USP

50 mL (54 gm)

50% w/w Aqueous Solution

For Irrigation Only

Not for Injection

Rx only Vial

Sterile. Non-pyrogenic.

Contains: 50% w/w dimethyl
sulfoxide in water for injection.

Usual Dosage: See
accompanying prescribing
information.

Store at 20° to 25°C (68° to 77°F).
[See USP Controlled Room
Temperature.]

Protect from strong light.

Manufactured for:
Mylan Institutional LLC
Morgantown, WV 26505 U.S.A.

Manufactured by:
Mylan Institutional
Galway, Ireland
RIMSO-50 is a registered trademark of Mylan Teoranta, a Viatris Company.

MI:177:1C:R5

Mylan.com